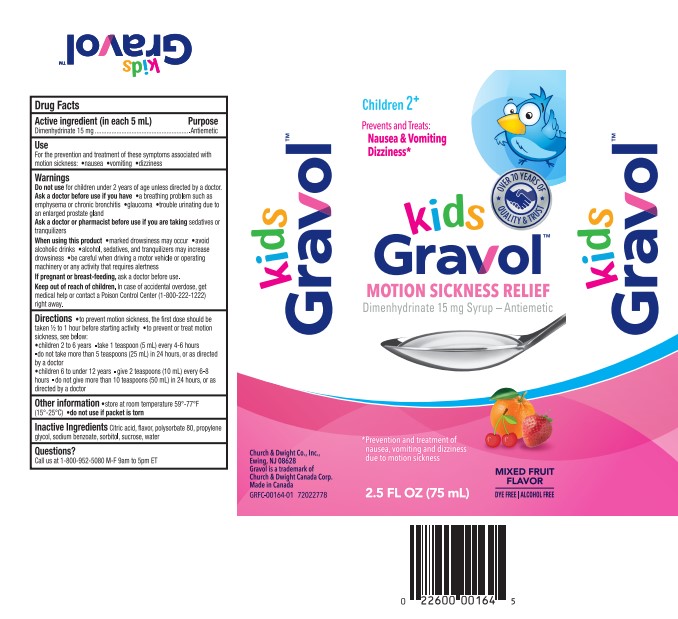 DRUG LABEL: Gravol
NDC: 10237-942 | Form: SYRUP
Manufacturer: Church & Dwight Co., Inc.
Category: otc | Type: HUMAN OTC DRUG LABEL
Date: 20240718

ACTIVE INGREDIENTS: DIMENHYDRINATE 15 mg/5 mL
INACTIVE INGREDIENTS: ANHYDROUS CITRIC ACID; SUCROSE; PROPYLENE GLYCOL; WATER; POLYSORBATE 80; SODIUM BENZOATE; SORBITOL

kids Gravol™ Motion Sickness Relief

Active ingredient (in each 5 mL)

Dimenhydrinate 15 mg

Purpose

Antiemetic

Use

For prevention and treatment of these symptoms associated with motion sickness:

- nausea
- vomiting
- dizziness

Warnings

Do not use

for children under 2 years of age unless directed by a doctor.

Ask a doctor before use if you have

- a breathing problem such as emphysema or chronic bronchitis
- glaucoma
- trouble urinating due to an enlarged prostate gland

Ask a doctor or pharmacist before use if you are taking

sedatives or tranquilizers

When using this product

- marked drowsiness may occur
- avoid alcoholic drinks
- alcohol, sedatives, and tranquilizers may increase dizziness
- be careful when driving a motor vehicle or operating machinery or any activity that requires alertness

If pregnant or breast-feeding,

ask a doctor before use.

Keep out of reach of children.

In case of accidental overdose, get medical help or contact a Poison Control Center (1-800-222-1222) right away.

Directions

- to prevent motion sickness, the first dose should be taken ½ to 1 hour before starting activity
- to prevent or treat motion sickness, see below:

children 2 to 6 years | - take 1 teaspoon (5 mL) every 4-6 hours - do not take more than 5 teaspoons (25 mL) in 24 hours, or as directed by a doctor
children 6 to under 12 years | - give 2 teaspoons (10 mL) every 6-8 hours - do not give more than 10 teaspoons (50 mL) in 24 hours, or as directed by a doctor

Other information

- store at room temperature 59º-77ºF (15º-25ºC)
- do not use if packet is torn

Inactive ingredients

Citric acid, flavor, polysorbate 80, propylene glycol, sodium benzoate, sorbitol, sucrose, water

Questions or comments?

1-800-952-5080 M-F 9am to 5pm ET

PRINCIPAL DISPLAY PANEL

OVER 70 YEARS OF

QUALITY & TRUST†

Children 2+

Prevents and Treats:

Nausea & Vomiting

Dizziness*

kids Gravol™

MOTION SICKNESS RELIEF

Dimenhydrinate 15 mg Syrup - Antiemetic

*Prevention and treatment of

nausea, vomiting and dizziness

due to motion sickness

MIXED FRUIT

FLAVOR

DYE FREE ALCOHOL FREE

2.5 FL OZ (75 mL)

Church & Dwight Co., Inc.,

Ewing, NJ 08628

Gravol is a trademark of

Church & Dwight Canada Corp.

Made in Canada

GRFC-00164-01 72022778